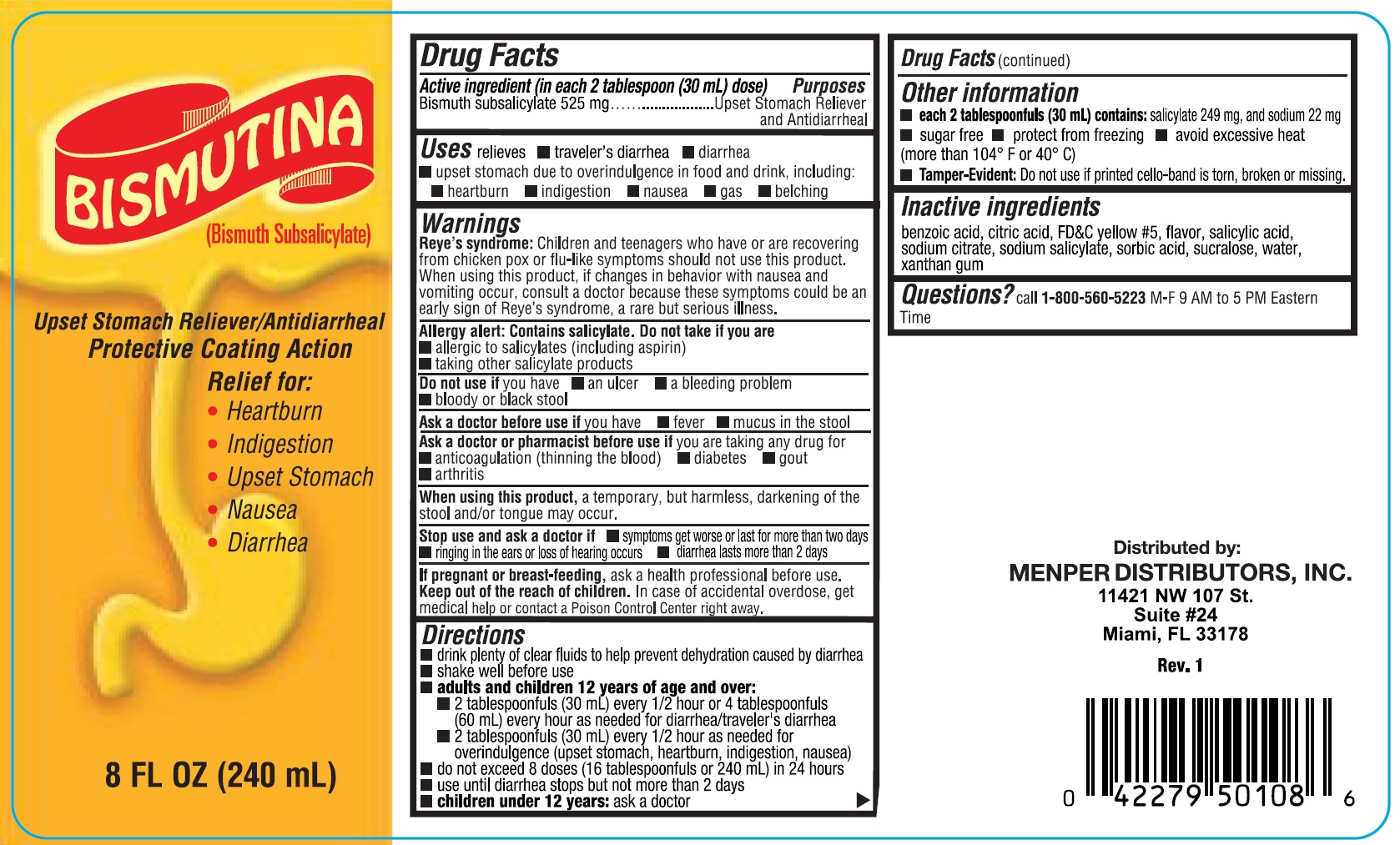 DRUG LABEL: Bismutina
NDC: 53145-475 | Form: LIQUID
Manufacturer: Menper Distributors, Inc.
Category: otc | Type: HUMAN OTC DRUG LABEL
Date: 20250722

ACTIVE INGREDIENTS: BISMUTH SUBSALICYLATE 525 mg/30 mL
INACTIVE INGREDIENTS: BENZOIC ACID; ANHYDROUS CITRIC ACID; FD&C YELLOW NO. 5; SALICYLIC ACID; SODIUM CITRATE; SODIUM SALICYLATE; SORBIC ACID; SUCRALOSE; WATER; XANTHAN GUM

Bismutina

Active Ingredients

Bismuth Subsalicylate 525 mg

Purpose

Upset Stomach Reliever and Antidiarrheal

Uses

relieves

- traveler's diarrhea
- diarrhea
- upset stomach due to overindulgence in food and drink, including:
- heartburn
- indigestion
- nausea
- gas
- belching

Warnings

Reye's syndrome: Children and teenagers who have or are recovering from chicken pox or flu-like symptoms should not use this product. When using this product, if changes in behavior with nausea and vomiting occur, consult a doctor because there symptoms could be an early sign of Reye's syndrome, a rare but serious illness.

Allergy alert: Contains salicylate. Do not take if you are

- allergic to salicylates (including aspirin)
- taking other salicylate products

Do not use if you have

- an ulcer
- a bleeding problem
- bloody or black stool

Ask a doctor before use if you have

- fever
- mucus in the stool

Ask a doctor or pharmacist before use if you are taking any drug for

- anticoagulation (thinning the blood)
- diabetes
- gout
- arthritis

When using this product, a temporary, but harmless, darking of the stool and/or tongue may occur.

Stop use and ask a doctor if

- symptoms get worse or last for more than two days
- ringing in the ears or loss of hearing occurs
- diarrhea lasts more than 2 days

PREGNANCY OR BREAST FEEDING

If pregnant or breast-feeding, ask a health professional before use.

Keep out of reach of children. In case of accidental overdose, get medical help or contact a Poison Control Center right away.

Directions

- drink plenty of clear fluids to help prevent dehydration cause by diarrhea
- shake well before use
- adults and children 12 years of age and over:
- 2 tablespoonfuls (30 mL) every 1/2 hour or 4 tablespoonfuls (60 mL) every hour as needed for diarrhea/traveler's diarrhea
- 2 tablespoonfuls (30 mL) every 1/2 hour as needed for overindulgence (upset stomach, heartburn, indigestion, nausea)
- do not exceed 8 doses (16 tablesproonfuls or 240 mL) in 24 hours
- use until diarrhea stops but not more than 2 days
- Children under 12 years: ask a doctor

Inactive ingredients

benzoic acid, citric acid, FD&C yellow #5, flavor, salicylic acid, sodium citrate, sodium salicylate, sorbic acid, sucralose, water, xanthan gum

QUESTIONS

Questions? call 1-800-560-5223 M-F 9 AM to 5 PM Eastern Time